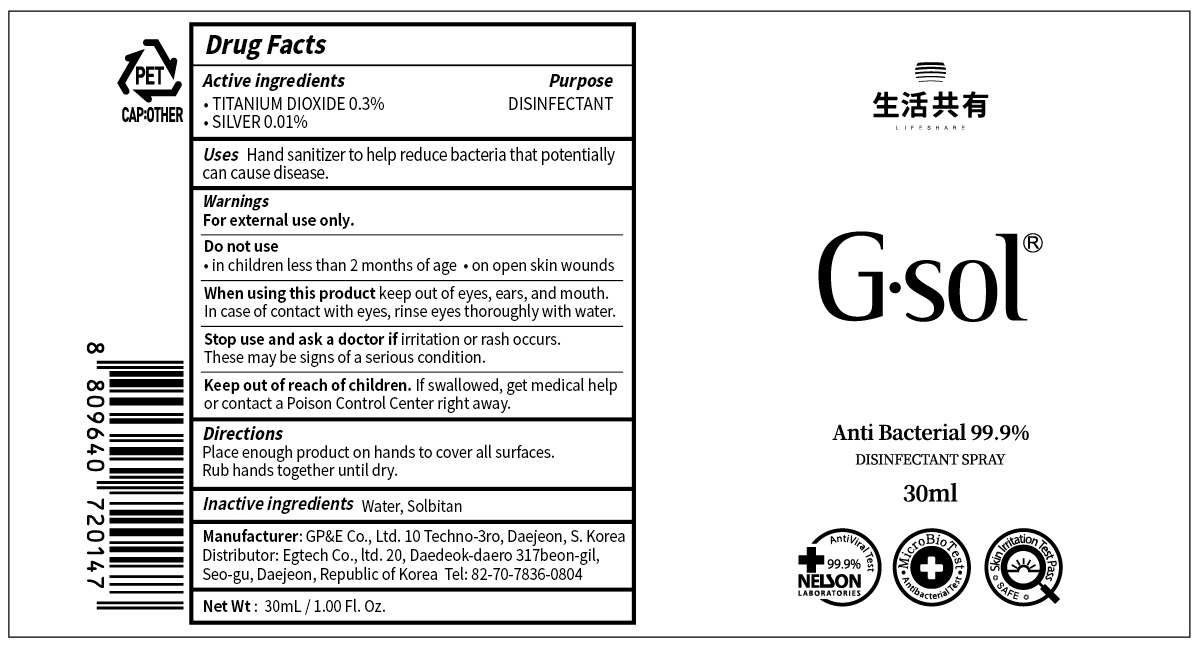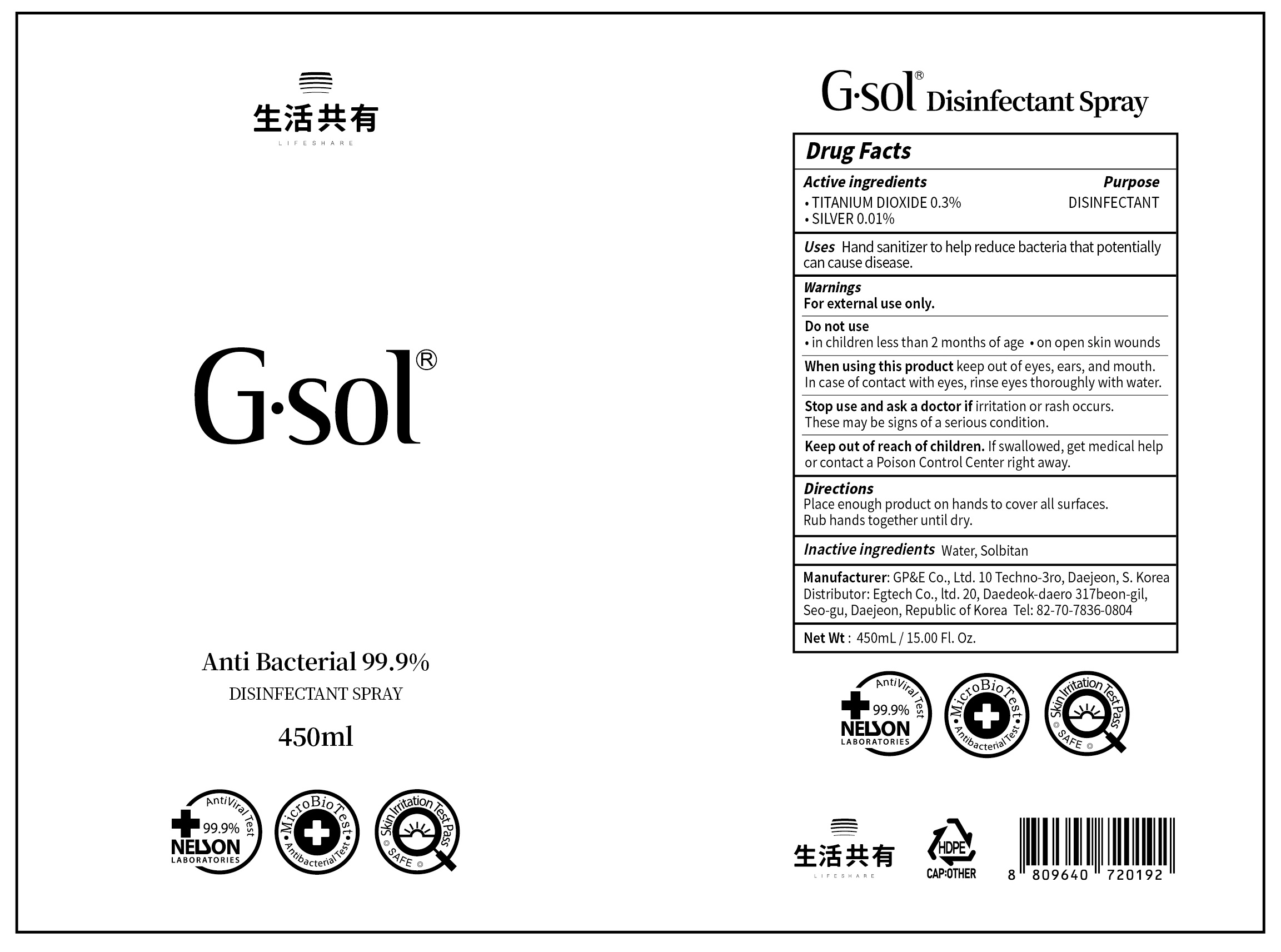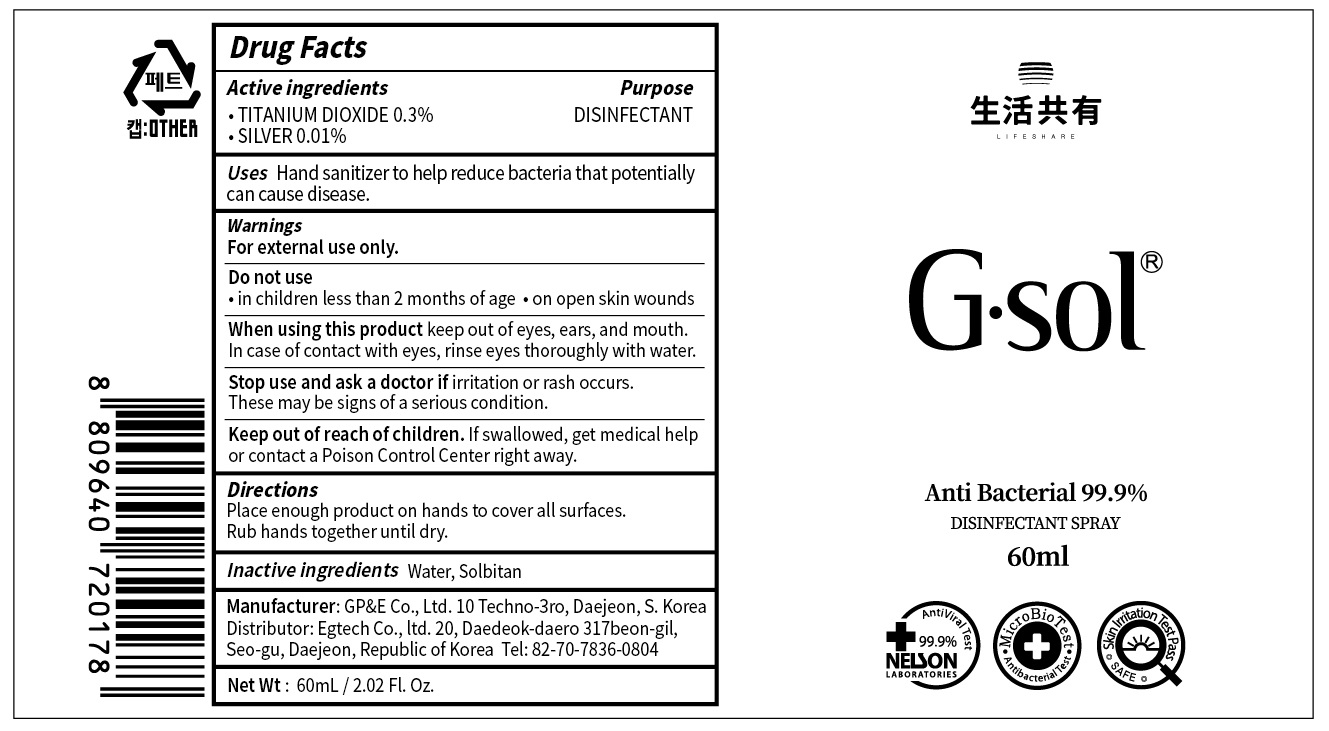 DRUG LABEL: G SOL
NDC: 76767-020 | Form: SPRAY
Manufacturer: Egtech co., Ltd.
Category: otc | Type: HUMAN OTC DRUG LABEL
Date: 20200519

ACTIVE INGREDIENTS: TITANIUM DIOXIDE 0.3 g/100 mL; SILVER 0.01 g/100 mL
INACTIVE INGREDIENTS: Water; SORBITAN

ACTIVE INGREDIENT

TITANIUM DIOXIDE 0.3%
SILVER 0.01%

INACTIVE INGREDIENT

Water, Sorbitan

PURPOSE

DISINFECTANT

WARNINGS

For external use only.
--------------------------------------------------------------------------------------------------------
Do not use
• in children less than 2 months of age
• on open skin wounds
--------------------------------------------------------------------------------------------------------
When using this product keep out of eyes, ears, and mouth. In case of contact with eyes, rinse eyes thoroughly with water.
--------------------------------------------------------------------------------------------------------
Stop use and ask a doctor if irritation or rash occurs. These may be signs of a serious condition.

KEEP OUT OF REACH OF CHILDREN

If swallowed, get medical help or contact a Poison Control Center right away.

Uses

Hand sanitizer to help reduce bacteria that potentially can cause disease.

Directions

Place enough product on hands to cover all surfaces. Rub hands together until dry.